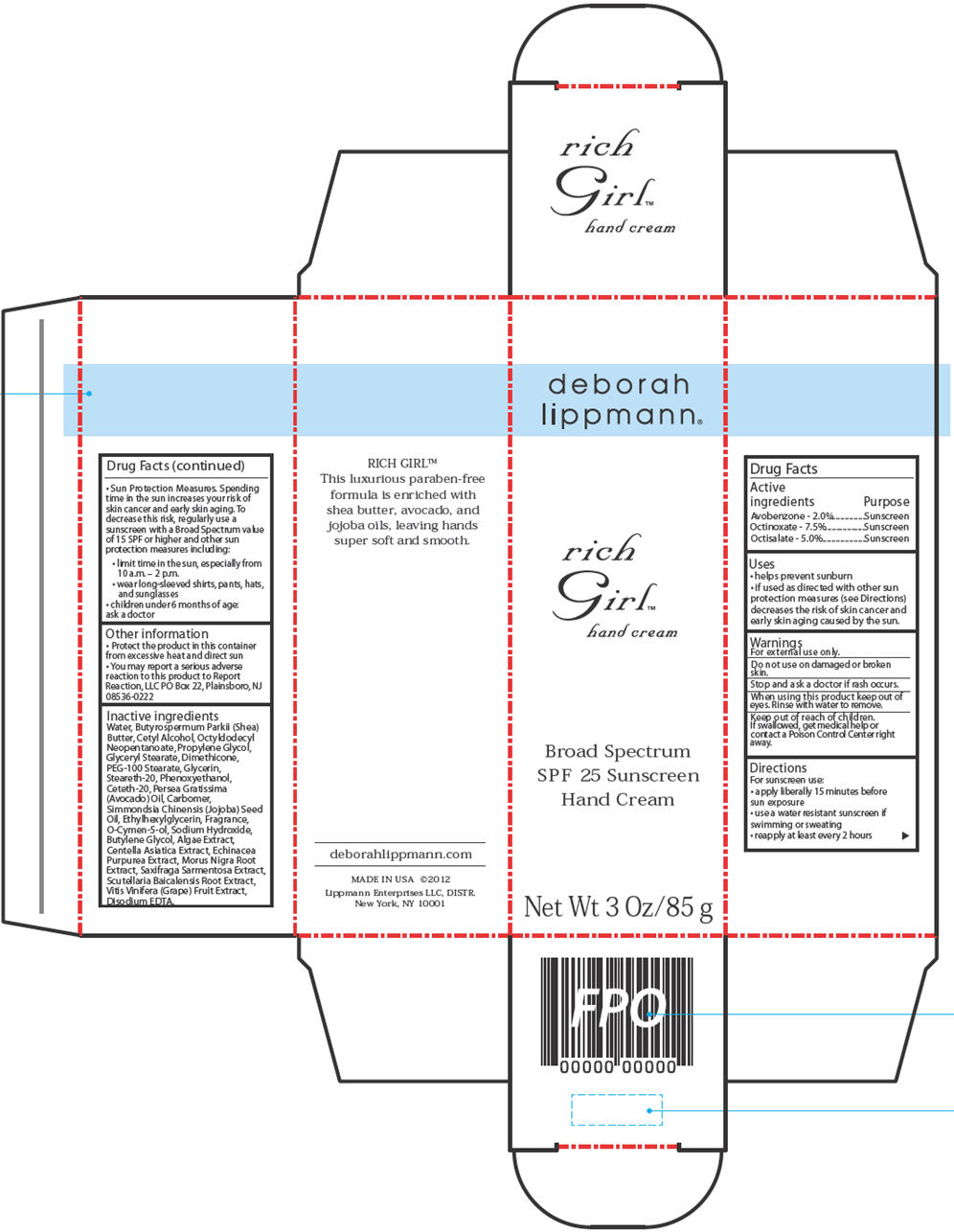 DRUG LABEL: RICH GIRL HAND SPF 25
NDC: 59735-420 | Form: CREAM
Manufacturer: MANA PRODUCTS, INC.
Category: otc | Type: HUMAN OTC DRUG LABEL
Date: 20240822

ACTIVE INGREDIENTS: OCTINOXATE 7.5 g/100 g; AVOBENZONE 2 g/100 g; OCTISALATE 5 g/100 g
INACTIVE INGREDIENTS: SCUTELLARIA BAICALENSIS ROOT; GLYCERYL MONOSTEARATE; CETYL ALCOHOL; WATER; PROPYLENE GLYCOL; DIMETHICONE; PEG-100 STEARATE; PHENOXYETHANOL; AVOCADO OIL; BUTYLENE GLYCOL; CENTELLA ASIATICA; ECHINACEA PURPUREA; SAXIFRAGA STOLONIFERA LEAF; WINE GRAPE; EDETATE DISODIUM; GLYCERIN; SHEA BUTTER; OCTYLDODECYL NEOPENTANOATE; STEARETH-20; CETETH-20; JOJOBA OIL; ETHYLHEXYLGLYCERIN; O-CYMEN-5-OL; SODIUM HYDROXIDE; MORUS NIGRA ROOT

RICH GIRL HAND

ACTIVE INGREDIENTS

Avobenzone 2 %
Octinoxate 7.5 %
Octisalate 5 %

PURPOSE

Sunscreen
Sunscreen
Sunscreen

USES

Helps prevent sunburn.
If used as directed with other sun protection measures (see Directions), decreases the risk of skin cancer and early skin aging caused by the sun.

WARNINGS

For external use only.
Do not use on damaged or broken skin.
When using this product keep out of eyes. Rinse with water to remove.

DIRECTIONS

For sunscreen use:
apply liberally 15 minutes before sun exposure
use a water resistant sunscreen if swimming or sweating
reapply at least every 2 hours
Sun Protection Measures. Spending time in the sun increases your risk of skin cancer and early skin aging. To decrease this risk, regularly use a sunscreen with a Broad Spectrumvalue of 15 SPF or higher and other sun protection measures including:
limit time in the sun, especially from 10 a.m. – 2 p.m.
wear long-sleeved shirts, pants, hats, and sunglasses
children under 6 months of age: ask a doctor

OTHER INFORMATION

Protect the product in this container from excessive heat and direct sun
You may report a serious adverse reaction to this product to Report Reaction, LLC PO Box 22, Plainsboro, NJ 08536-0222

INACTIVE INGREDIENTS

Water, Butyrospermum Parkii (Shea) Butter, Cetyl Alcohol, Octyldodecyl Neopentanoate, Propylene Glycol, Glyceryl Stearate, Dimethicone, PEG-100 Stearate, Glycerin, Steareth-20,Phenoxyethanol, Ceteth-20, Persea Gratissima (Avocado) Oil, Carbomer, Simmondsia Chinensis (Jojoba) Seed Oil, Ethylhexylglycerin, Fragrance, O-Cymen-5-ol, Sodium Hydroxide,Butylene Glycol, Algae Extract, Centella Asiatica Extract, Echinacea Purpurea Extract, Morus Nigra Root Extract, Saxifraga Sarmentosa Extract, Scutellaria Baicalensis Root Extract,Vitis Vinifera (Grape) Fruit Extract, Disodium EDTA.

Keep out of reach of children. If product is swallowed, get medical help or contact a Poison Control Center right away.

Stop use and ask a doctor if rash occurs

RECENT MAJOR CHANGES

dosage & admin update